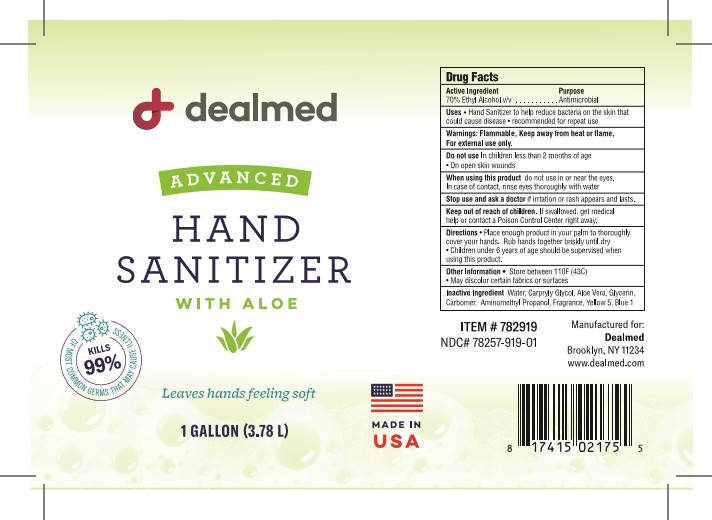 DRUG LABEL: Advanced Hand Sanitizer
NDC: 78257-919 | Form: GEL
Manufacturer: DEALMED MEDICAL SUPPLIES LLC
Category: otc | Type: HUMAN OTC DRUG LABEL
Date: 20201119

ACTIVE INGREDIENTS: ALCOHOL 70 mL/100 mL
INACTIVE INGREDIENTS: CAPRYLYL GLYCOL; GLYCERIN; WATER; AMINOMETHYLPROPANOL; FD&C YELLOW NO. 5; FRAGRANCE CLEAN ORC0600327; CARBOMER 940; FD&C BLUE NO. 1 ALUMINUM LAKE; ALOE VERA LEAF

Active Ingredient(s)

Ethyl Alcohol 70% v/v. Purpose: Antiseptic

Purpose

Antiseptic, Hand Sanitizer

Use

Hand Sanitizer to help reduce bacteria on the skin that can cause disease. recommended for repeat use

Warnings

Flammable. Keep away from heat or flame, For external use only.

Do not use

- in children less than 2 months of age
- on open skin wounds

Do not use in or near the eyes. in case of contact, rinse thorougly with water.

Stop use and ask a doctor if irritation or rash appears and lasts.

Keep out of reach of children. If swallowed, get medical help or contact a Poison Control Center right away.

Directions

- Place enough product in your palm to thorougly cover your hands. Rub hands together until dry.
- Children under 6 years of age should be supervised when using this product.

Other information

- Store below 110FC (43C)
- May discolor certain fabrics or surfaces.

Inactive ingredients

Water, Carprylyl Glycol, Aloe Vera, Glycerin, Carbomer, Aminomethyl Propanol, Fragrance, Yellow 5 and Blue 1.

Package Label - Principal Display Panel

3.78 L NDC: 78257-919-01